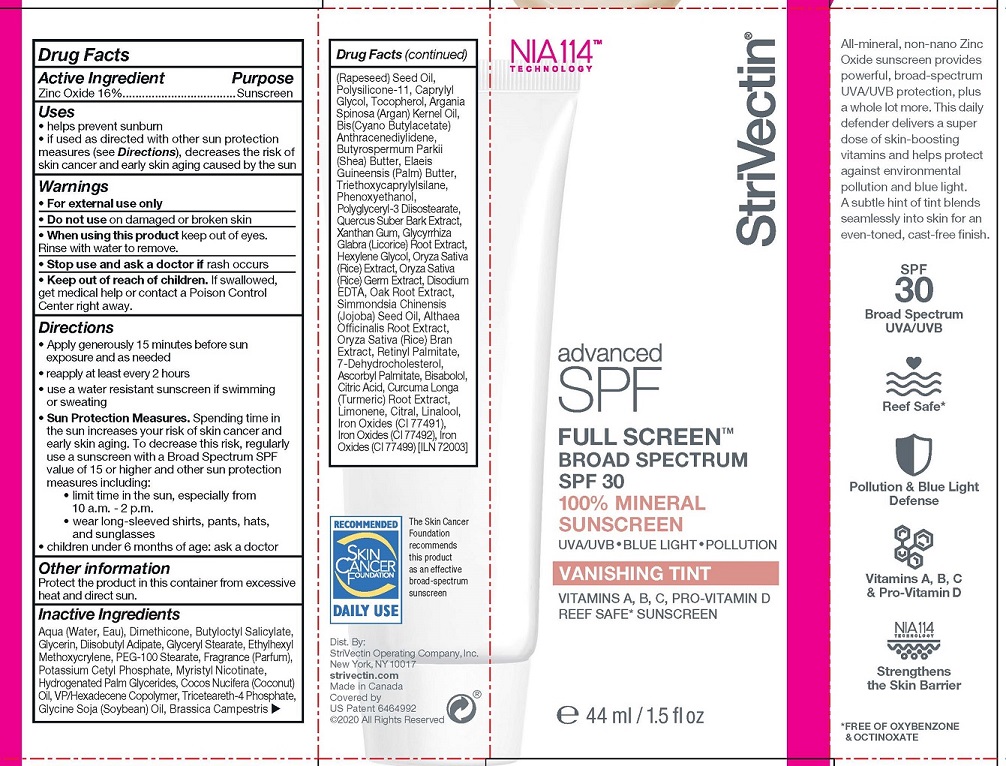 DRUG LABEL: StriVectin Advanced SPF Full Screen
NDC: 54291-053 | Form: LOTION
Manufacturer: Canadian Custom Packaging Company
Category: otc | Type: HUMAN OTC DRUG LABEL
Date: 20241211

ACTIVE INGREDIENTS: ZINC OXIDE 16 g/100 mL
INACTIVE INGREDIENTS: WATER; DIMETHICONE; BUTYLOCTYL SALICYLATE; GLYCERIN; DIISOBUTYL ADIPATE; ETHYLHEXYL METHOXYCRYLENE; GLYCERYL STEARATE/PEG-100 STEARATE; POTASSIUM CETYL PHOSPHATE; MYRISTYL NICOTINATE; HYDROGENATED PALM GLYCERIDES; COCONUT OIL; VINYLPYRROLIDONE/HEXADECENE COPOLYMER; TRICETEARETH-4 PHOSPHATE; SOYBEAN OIL; CANOLA OIL; DIMETHICONE/VINYL DIMETHICONE CROSSPOLYMER (SOFT PARTICLE); CAPRYLYL GLYCOL; TOCOPHEROL; ARGAN OIL; CYANOMETHYLACETATE; SHEA BUTTER; ELAEIS GUINEENSIS FRUIT BUTTER; TRIETHOXYCAPRYLYLSILANE; PHENOXYETHANOL; POLYGLYCERYL-3 DIISOSTEARATE; QUERCUS SUBER BARK; XANTHAN GUM; GLYCYRRHIZA GLABRA; HEXYLENE GLYCOL; ORYZA SATIVA WHOLE; EDETATE DISODIUM; QUERCUS PETRAEA WHOLE; JOJOBA OIL; ALTHAEA OFFICINALIS ROOT; VITAMIN A PALMITATE; 7-DEHYDROCHOLESTEROL; ASCORBYL PALMITATE; .ALPHA.-BISABOLOL, (+)-; ANHYDROUS CITRIC ACID; CURCUMA LONGA WHOLE; LIMONENE, (+)-; CITRAL; FERRIC OXIDE RED; FERROSOFERRIC OXIDE; FERRIC OXIDE YELLOW

StriVectin Advanced SPF Full Screen - Tinted

ACTIVE INGREDIENTS

ZINC OXIDE 16%

PURPOSE

Sunscreen

USES

- helps prevent sunburn
- if used as directed with other sun protection measures (see Directions), decreases the risk of skin cancer and early skin aging caused by the sun

WARNINGS

- For external use only
- Do not use on damaged or broken skin
- When using this product keep out of eyes. Rinse with water to remove.
- Stop use and ask a doctor if rash occurs

Keep out of reach of children.

If swallowed, get medical help or contact
a Poison Control Center right away.

- Keep out of reach of children. If swallowed, get medical help or contact a Poison Control Center right away.

DIRECTIONS

- Apply generously 15 minutes before sun exposure and as needed
- reapply at least every 2 hours
- use a water resistant sunscreen if swimming or sweating
- Sun Protection Measures. Spending time inthe sun increases your risk of skin cancer andearly skin aging. To decrease this risk, regularly use a sunscreen with a Broad Spectrum SPFvalue of 15 or higher and other sun protectionmeasures including:
- limit time in the sun, especially from 10 a.m. - 2 p.m.
- wear long-sleeved shirts, pants, hats,and sunglasses
- children under 6 months of age: ask a doctor

OTHER INFORMATION

Protect the product in this container from excessive heat and direct sun.

INACTIVE INGREDIENTS

Aqua (Water, Eau), Dimethicone, Butyloctyl Salicylate, Glycerin, Diisobutyl Adipate, Glyceryl Stearate, Ethylhexyl Methoxycrylene, PEG-100 Stearate, Fragrance (Parfum), Potassium Cetyl Phosphate, Myristyl Nicotinate, Hydrogenated Palm Glycerides, Cocos Nucifera (Coconut) Oil, VP/Hexadecene Copolymer, Triceteareth-4 Phosphate, Glycine Soja (Soybean) Oil, Brassica Campestris (Rapeseed) Seed Oil, Polysilicone-11, Caprylyl Glycol, Tocopherol, Argania Spinosa (Argan) Kernel Oil, Bis(Cyano Butylacetate) Anthracenediylidene, Butyrospermum Parkii (Shea) Butter, Elaeis Guineensis (Palm) Butter, Triethoxycaprylylsilane, Phenoxyethanol, Polyglyceryl-3 Diisostearate, Quercus Suber Bark Extract, Xanthan Gum, Glycyrrhiza Glabra (Licorice) Root Extract, Hexylene Glycol, Oryza Sativa (Rice) Extract, Oryza Sativa (Rice) Germ Extract, Disodium EDTA, Oak Root Extract, Simmondsia Chinensis (Jojoba) Seed Oil, Althaea Officinalis Root Extract, Oryza Sativa (Rice) Bran Extract, Retinyl Palmitate, 7-Dehydrocholesterol, Ascorbyl Palmitate, Bisabolol, Citric Acid, Curcuma Longa (Turmeric) Root Extract, Limonene, Citral, Linalool, Iron Oxides (CI 77491), Iron Oxides (CI 77492), Iron Oxides (CI 77499)